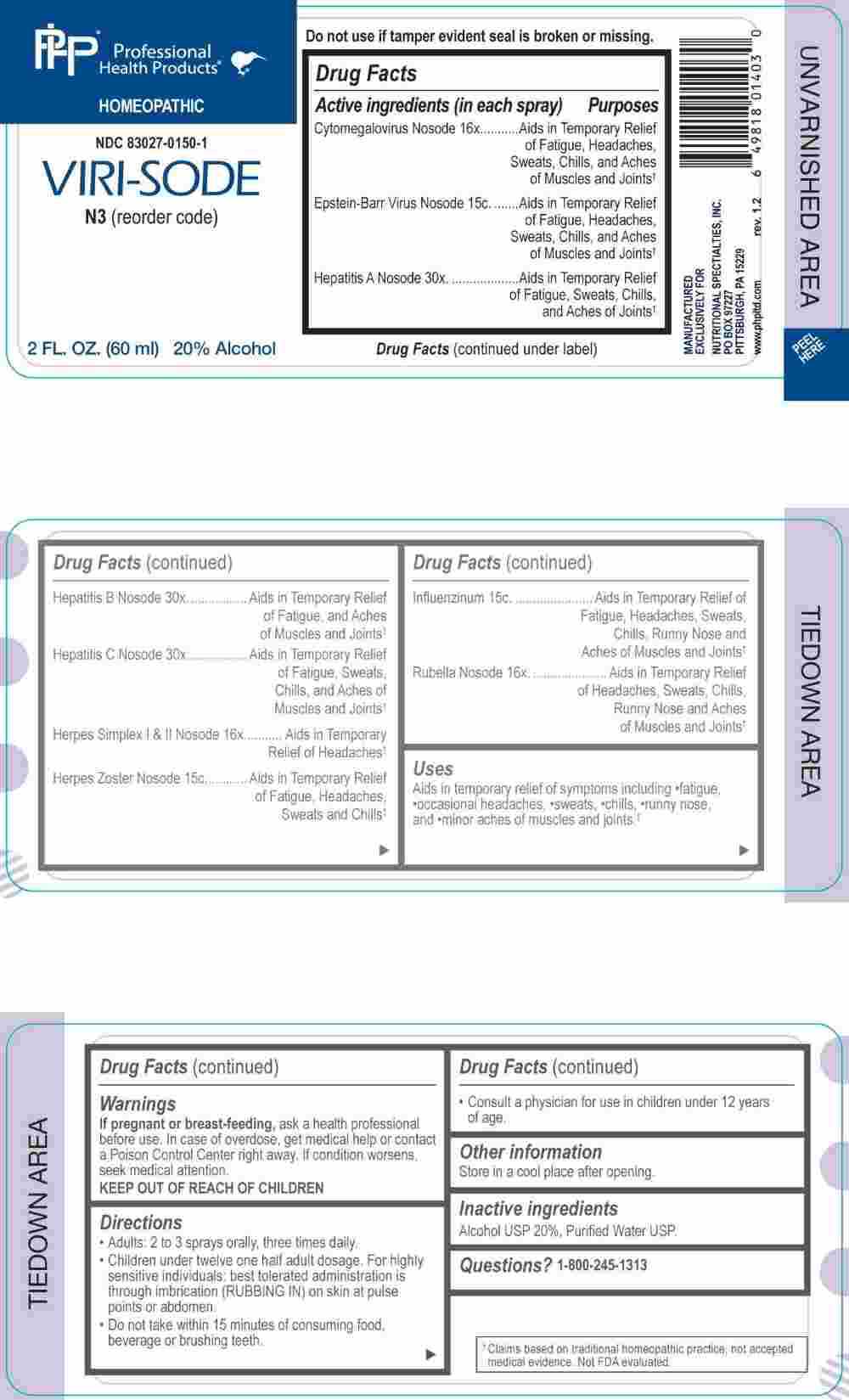 DRUG LABEL: Viri Sode
NDC: 83027-0150 | Form: SPRAY
Manufacturer: Nutritional Specialties, Inc.
Category: homeopathic | Type: HUMAN OTC DRUG LABEL
Date: 20250603

ACTIVE INGREDIENTS: HUMAN HERPESVIRUS 5 16 [hp_X]/1 mL; HUMAN HERPESVIRUS 1 16 [hp_X]/1 mL; HUMAN HERPESVIRUS 2 16 [hp_X]/1 mL; INFLUENZA A VIRUS A/VICTORIA/4897/2022 IVR-238 (H1N1) ANTIGEN (FORMALDEHYDE INACTIVATED) 15 [hp_C]/1 mL; INFLUENZA A VIRUS A/THAILAND/8/2022 IVR-237 (H3N2) ANTIGEN (FORMALDEHYDE INACTIVATED) 15 [hp_C]/1 mL; INFLUENZA B VIRUS B/AUSTRIA/1359417/2021 BVR-26 WHOLE 15 [hp_C]/1 mL; INFLUENZA B VIRUS B/PHUKET/3073/2013 BVR-1B WHOLE 15 [hp_C]/1 mL; RUBELLA VIRUS 16 [hp_X]/1 mL; HEPATITIS A VIRUS 30 [hp_X]/1 mL; HEPATITIS B VIRUS 30 [hp_X]/1 mL; HEPATITIS C VIRUS 30 [hp_X]/1 mL; HUMAN HERPESVIRUS 4 15 [hp_C]/1 mL; HUMAN HERPESVIRUS 3 15 [hp_C]/1 mL
INACTIVE INGREDIENTS: WATER; ALCOHOL

DRUG FACTS:

ACTIVE INGREDIENTS:

Cytomegalovirus Nosode 16X, Epstein Barr Virus Nosode 15C, Hepatitis A Nosode 30X, Hepatitis B Nosode 30X, Hepatitis C Nosode 30X, Herpes Simplex I & II Nosode 16X, Herpes Zoster Nosode 15C, Influenzinum 15C, Rubella Nosode 16X.

PURPOSE:

Cytomegalovirus Nosode – Aids in Temporary Relief of Fatigue, Headaches, Sweats, Chills, and Aches of Muscles and Joints,† Epstein Barr Virus Nosode - Aids in Temporary Relief of Fatigue, Headaches, Sweats, Chills, and Aches of Muscles and Joints,† Hepatitis A Nosode - Aids in Temporary Relief of Fatigue, Sweats, Chills, and Aches of Joints,† Hepatitis B Nosode – Aids in Temporary Relief of Fatigue, and Aches of Muscles and Joints,† Hepatitis C Nosode - Aids in Temporary Relief of Fatigue, Sweats, Chills, and Aches of Muscles and Joints,† Herpes Simplex I & II Nosode – Aids in Temporary Relief of Headaches,† Herpes Zoster Nosode – Aids in Temporary Relief of Fatigue, Headaches, Sweats and Chills,† Influenzinum - Aids in Temporary Relief of Fatigue, Headaches, Sweats, Chills, Runny Nose and Aches of Muscles and Joints,† Rubella Nosode - Aids in Temporary Relief of Headaches, Sweats, Chills, Runny Nose and Aches of Muscles and Joints†

†Claims based on traditional homeopathic practice, not accepted medical evidence. Not FDA evaluated.

USES:

Aids in temporary relief of symptoms including fatigue, occasional headaches, sweats, chills, runny nose, and minor aches of muscles and joints.†

†Claims based on traditional homeopathic practice, not accepted medical evidence. Not FDA evaluated.

WARNINGS:

If pregnant or breast-feeding, ask a health professional before use.

In case of overdose, get medical help or contact a Poison Control Center right away.

If condition worsens, seek medical attention.

KEEP OUT OF REACH OF CHILDREN

Do not use if tamper evident seal is broken or missing.

Store in a cool place after opening

KEEP OUT OF REACH OF CHILDREN:

In case of overdose, get medical help or contact a Poison Control Center right away.

DIRECTIONS:

• Adults: 2 to 3 sprays orally, three times daily.

• Children under twelve one half adult dosage. For highly sensitive individuals: best tolerated administration is through imbrication (RUBBING IN) on skin at pulse points or abdomen.

• Do not take within 15 minutes of consuming food, beverage or brushing teeth.

Consult a physician for use in children under 12 years of age.

INACTIVE INGREDIENTS:

Alcohol USP 20%, Purified Water USP.

QUESTIONS:

MANUFACTURED EXCLUSIVELY FOR

NUTRITIONAL SPECIALTIES, INC.

PO BOX 97227

PITTSBURG, PA 15229

www.phpltd.com

1-800245-1313

PACKAGE LABEL DISPLAY:

Professional

Health Products

HOMEOPATHIC

NDC 83027-0150-1

VIRI-SODE

2 FL. OZ (60 ml)